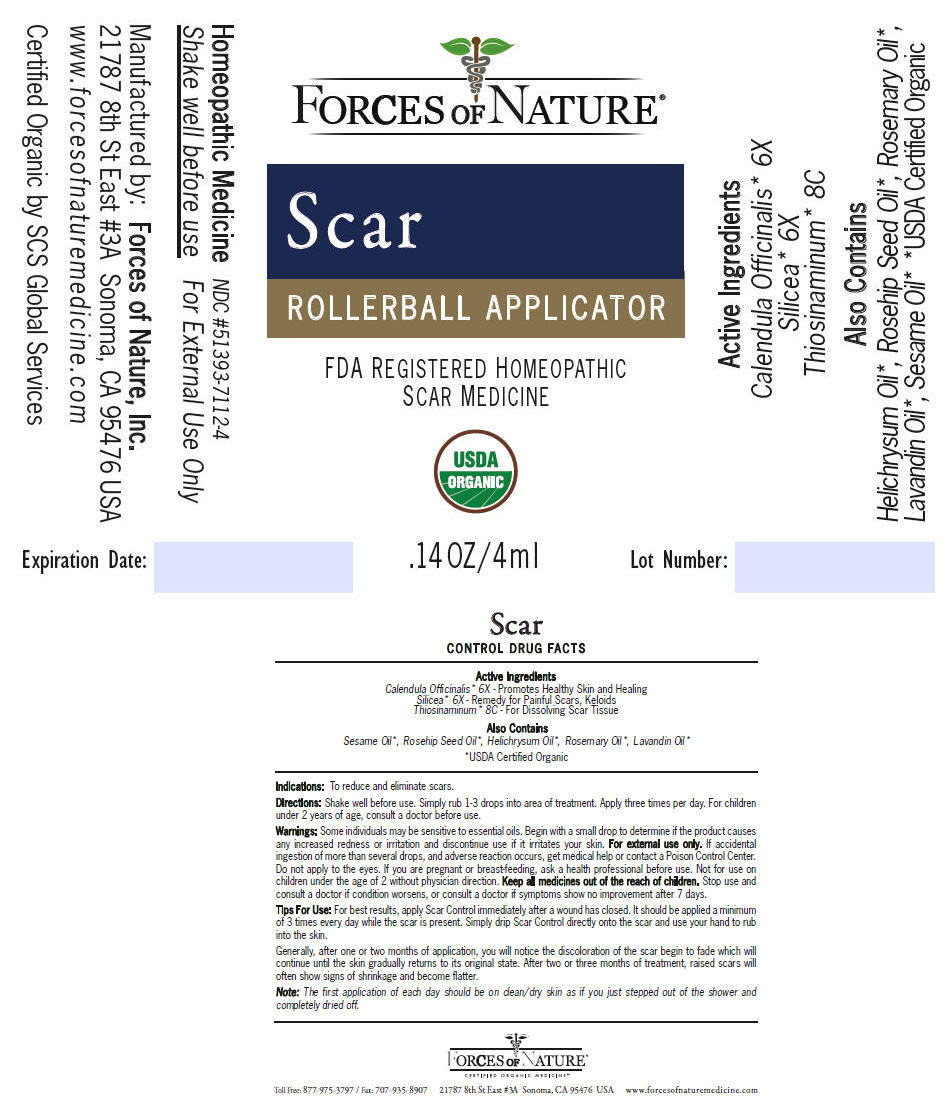 DRUG LABEL: Scar Control
NDC: 51393-7112 | Form: SOLUTION/ DROPS
Manufacturer: Forces of Nature
Category: homeopathic | Type: HUMAN OTC DRUG LABEL
Date: 20210514

ACTIVE INGREDIENTS: Calendula Officinalis Flowering Top 6 [hp_X]/1000 mL; Allylthiourea 8 [hp_C]/1000 mL; Silicon Dioxide 6 [hp_X]/1000 mL
INACTIVE INGREDIENTS: Lavandin Oil; Helichrysum Italicum Flower; Rosemary Oil; Sesame Oil; Rosa Moschata Oil

Scar CONTROL

DRUG FACTS

ACTIVE INGREDIENT

PURPOSE

Active Ingredients

Calendula Officinalis [USDA Certified Organic] 6X - Promotes Healthy Skin and Healing

Silicea 6X - Remedy for Painful Scars, Keloids

Thiosinaminum 8C - For Dissolving Scar Tissue

Also Contains

Sesame Oil, Rosehip Seed Oil, Helichrysum Oil, Rosemary Oil, Lavandin Oil

Indications

To reduce and eliminate scars.

Directions

Shake well before use. Simply rub 1-3 drops into area of treatment. Apply three times per day. For children under 2 years of age, consult a doctor before use.

Warnings

Some individuals may be sensitive to essential oils. Begin with a small drop to determine if the product causes any increased redness or irritation and discontinue use if it irritates your skin. For external use only. If accidental ingestion of more than several drops, and adverse reaction occurs, get medical help or contact a Poison Control Center. Do not apply to the eyes. If you are pregnant or breast-feeding, ask a health professional before use. Not for use on children under the age of 2 without physician direction.

KEEP OUT OF REACH OF CHILDREN

Keep all medicines out of the reach of children.

Stop use and consult a doctor if condition worsens, or consult a doctor if symptoms show no improvement after 7 days.

Tips For Use

For best results, apply Scar Control immediately after a wound has closed. It should be applied a minimum of 3 times every day while the scar is present. Simply drip Scar Control directly onto the scar and use your hand to rub into the skin.

Generally, after one or two months of application, you will notice the discoloration of the scar begin to fade which will continue until the skin gradually returns to its original state. After two or three months of treatment, raised scars will often show signs of shrinkage and become flatter.

Note: The first application of each day should be on clean/dry skin as if you just stepped out of the shower and completely dried off.

Manufactured by: Forces of Nature, Inc.
21787 8th St East #3A Sonoma, CA 95476 USA

PRINCIPAL DISPLAY PANEL - 4 ml Bottle Label

FORCES OF NATURE®

Scar
ROLLERBALL APPLICATOR

FDA REGISTERED HOMEOPATHIC
SCAR MEDICINE

USDA
ORGANIC

.14 OZ/4ml
Lot Number: